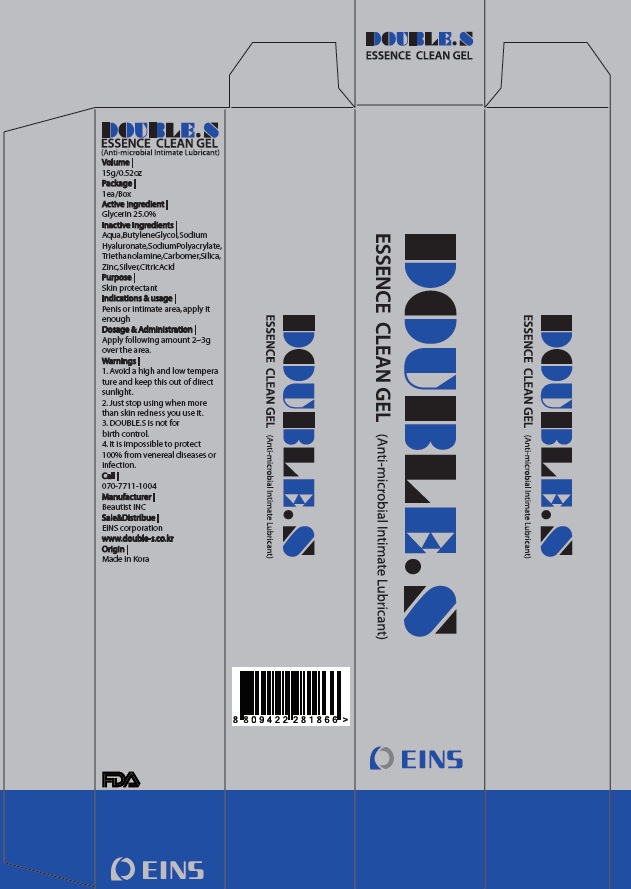 DRUG LABEL: Double S Essence Clean
NDC: 70654-010 | Form: GEL
Manufacturer: EINS CORPORATION
Category: otc | Type: HUMAN OTC DRUG LABEL
Date: 20160510

ACTIVE INGREDIENTS: Glycerin 3.75 g/15 g
INACTIVE INGREDIENTS: WATER; Butylene Glycol

ACTIVE INGREDIENT

Active Ingredient: Glycerin 25.0%

INACTIVE INGREDIENT

Inactive Ingredients: Aqua, Butylene Glycol, Sodium Hyaluronate, Sodium Polyacrylate, Triethanolamine, Carbomer, Silica, Zinc, Silver, Citric Acid

PURPOSE

Purpose: Skin protectant

WARNINGS

Warnings: Avoid a high and low temperature and keep this out of direct sunlight. Just stop using when more than skin redness you use it. DOUBLE.S is not for birth control. It is impossible to protect 100% from venereal diseases or infection.

KEEP OUT OF REACH OF CHILDREN

INDICATIONS & USAGE

Indications & usage: Penis or intimate area, apply it enough.

DOSAGE & ADMINISTRATION

Dosage & Administration: Apply following amount 2~3g over the area